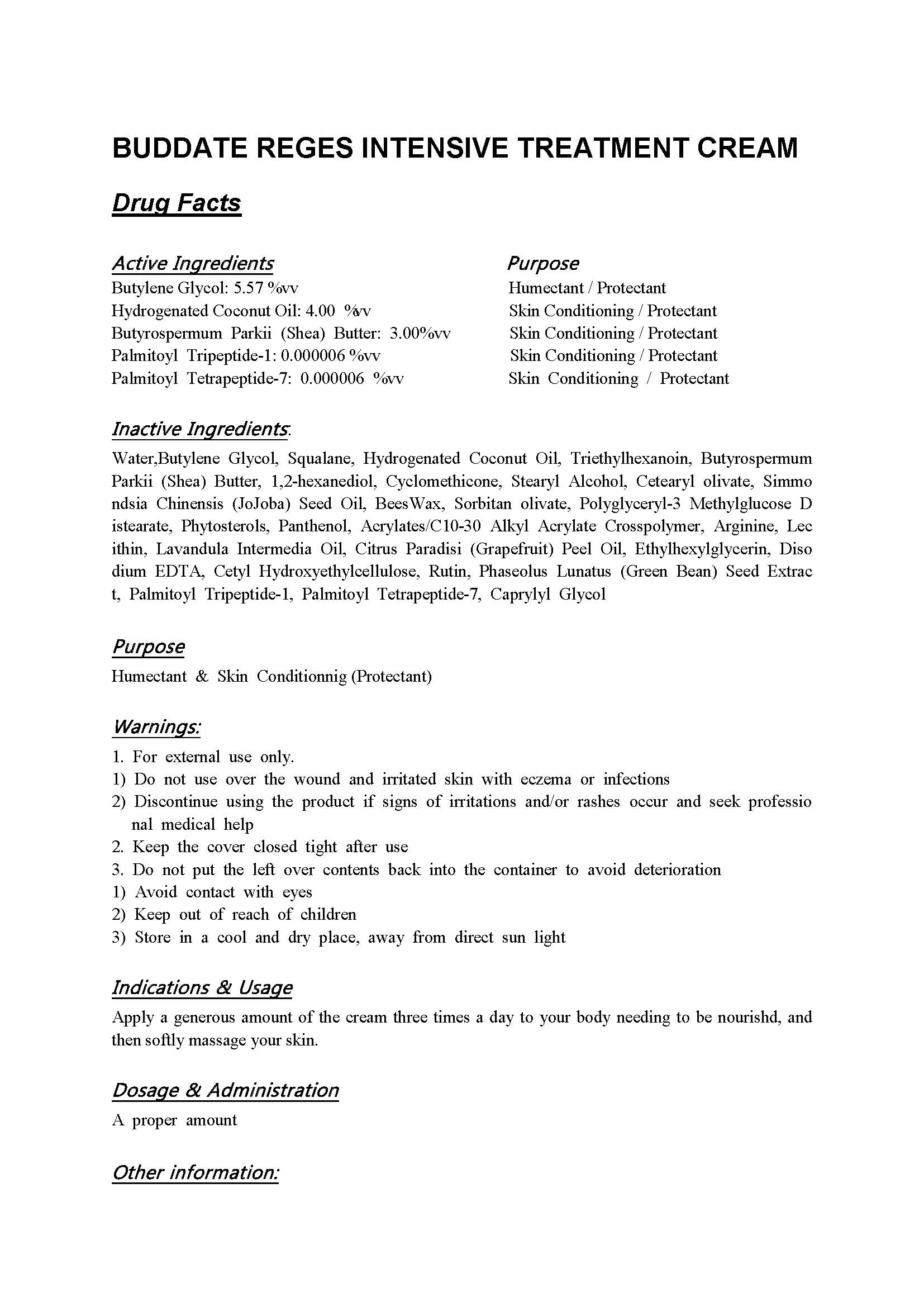 DRUG LABEL: BUDDATE REGES INTENSIVE TREATMENT
NDC: 71173-3000 | Form: CREAM
Manufacturer: BUDDATE Co Ltd
Category: otc | Type: HUMAN OTC DRUG LABEL
Date: 20251130

ACTIVE INGREDIENTS: PALMITOYL TETRAPEPTIDE-7 0.000006 g/100 mL; SHEA BUTTER 3 g/100 mL; PALMITOYL TRIPEPTIDE-1 0.000006 g/100 mL; BUTYLENE GLYCOL 5.57 g/100 mL; HYDROGENATED COCONUT OIL 4 g/100 mL
INACTIVE INGREDIENTS: WATER

Drug Facts

ACTIVE INGREDIENT

Butylene Glycol: 5.57 %vv

Hydrogenated Coconut Oil: 4.00 %vv

Butyrospermum Parkii (Shea) Butter: 3.00%vv

Palmitoyl Tripeptide-1: 0.000006 %vv

Palmitoyl Tetrapeptide-7: 0.000006 %vv

INACTIVE INGREDIENT

Water, Squalane, Triethylhexanoin, 1,2-hexanediol, Cyclomethicone, Stearyl Alcohol, Cetearyl olivate, Simmondsia Chinensis (JoJoba) Seed Oil, BeesWax, Sorbitan olivate, Polyglyceryl-3 Methylglucose Distearate, Phytosterols, Panthenol, Acrylates/C10-30 Alkyl Acrylate Crosspolymer, Arginine, Lecithin, Lavandula Intermedia Oil, Citrus Paradisi (Grapefruit) Peel Oil, Ethylhexylglycerin, Disodium EDTA, Cetyl Hydroxyethylcellulose, Rutin, Phaseolus Lunatus (Green Bean) Seed Extract, Caprylyl Glycol

PURPOSE

Humectant & Skin Conditionnig (Protectant)

keep out of reach of the children

INDICATIONS AND USAGE

Apply a generous amount of the cream three times a day to your body needing to be nourishd, and then softly massage your skin.

WARNINGS

1. For external use only.

1) Do not use over the wound and irritated skin with eczema or infections

2) Discontinue using the product if signs of irritations and/or rashes occur and seek professional medical help

2. Keep the cover closed tight after use

3. Do not put the left over contents back into the container to avoid deterioration

1) Avoid contact with eyes

2) Keep out of reach of children

3) Store in a cool and dry place, away from direct sun light

DOSAGE AND ADMINISTRATION

for external use only